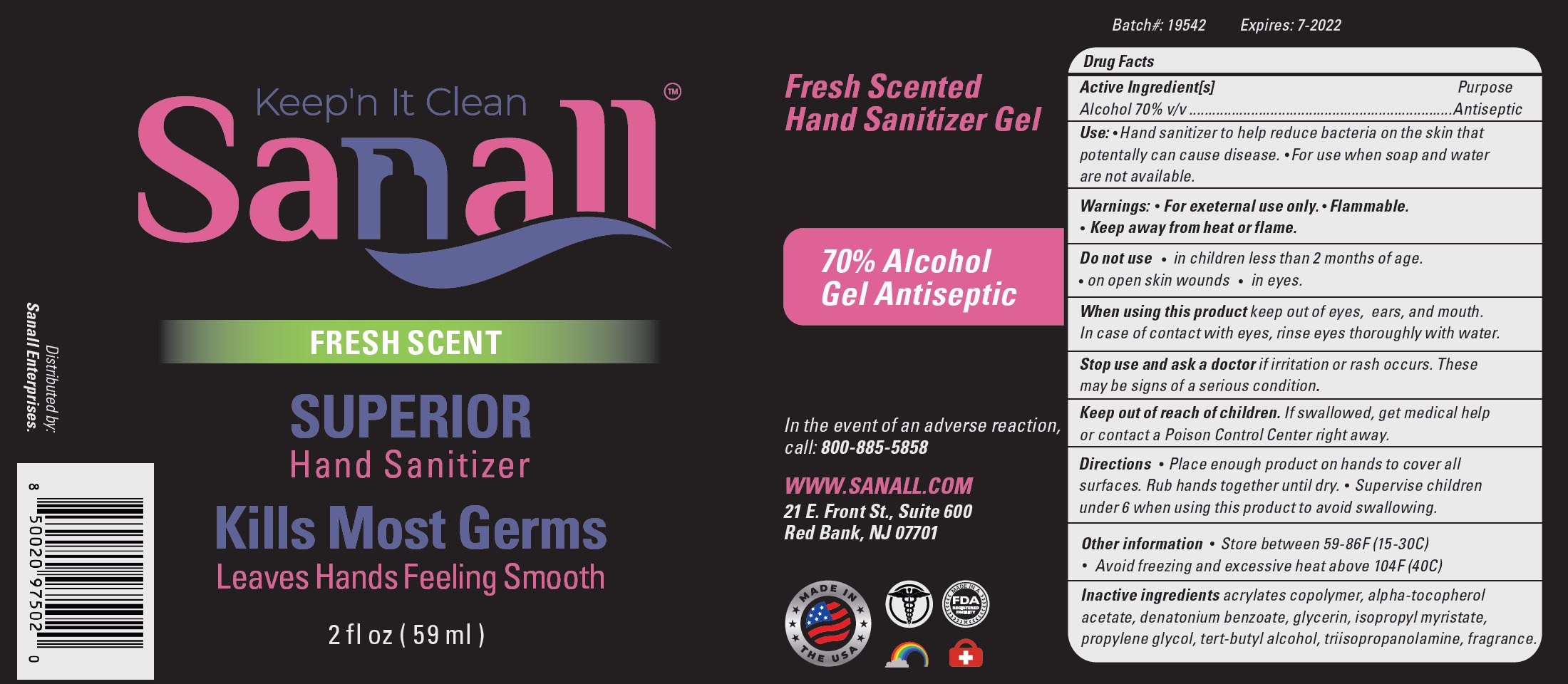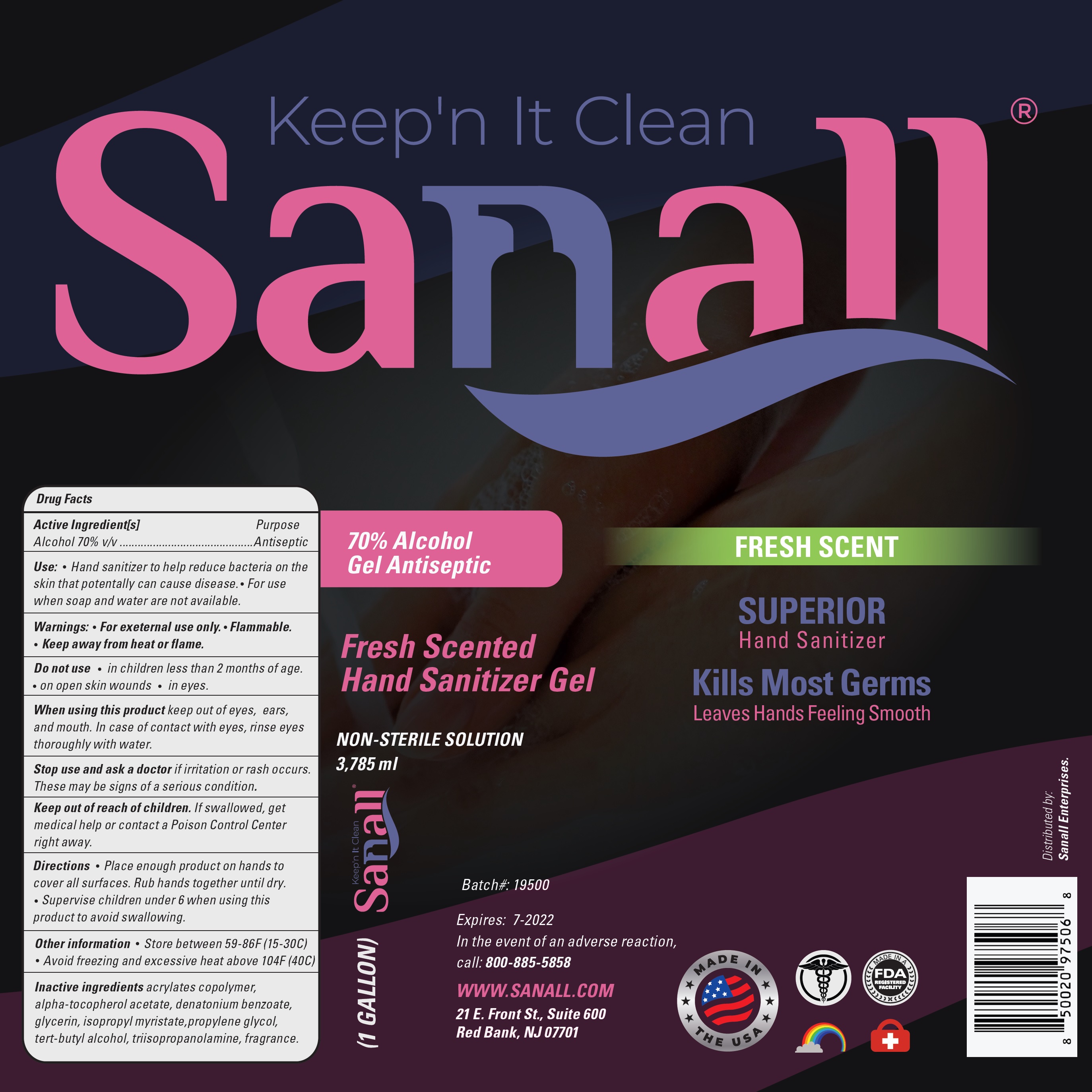 DRUG LABEL: Keep n It Clean Sanall Hand Sanitizer Fresh Scent
NDC: 79537-001 | Form: GEL
Manufacturer: Sanall Enterprises, LLC
Category: otc | Type: HUMAN OTC DRUG LABEL
Date: 20200817

ACTIVE INGREDIENTS: ALCOHOL 0.7 mL/1 mL
INACTIVE INGREDIENTS: .ALPHA.-TOCOPHEROL ACETATE; DENATONIUM BENZOATE; GLYCERIN; ISOPROPYL MYRISTATE; PROPYLENE GLYCOL; TERT-BUTYL ALCOHOL; TRIISOPROPANOLAMINE; BUTYL ACRYLATE/METHYL METHACRYLATE/METHACRYLIC ACID COPOLYMER (18000 MW)

Keep n It Clean Sanall Hand Sanitizer Fresh Scent

Active Ingredient[s]

Alcohol 70% v/v

Purpose

Antiseptic

Use:

- Hand sanitizer to help reduce bacteria on the skin that potentally can cause disease.
- For use when soap and water are not available.

Warnings:

- For exeternal use only.
- Flammable.
- Keep away from heat or flame.

Do not use

- in children less than 2 months of age.
- on open skin wounds
- in eyes.

When using this product

keep out of eyes, ears, and mouth. In case of contact with eyes, rinse eyes thoroughly with water

Stop use and ask a doctor

if irritation or rash occurs. These may be signs of a serious condition.

Keep out of reach of children.

If swallowed, get medical help or contact a Poison Control Center right away.

Directions

- Place enough product on hands to cover all surfaces. Rub hands together until dry.
- Supervise children under 6 when using this product to avoid swallowing.

Other information

- Store between 59-86F (15-30C)
- Avoid freezing and excessive heat above 104F (40C)

Inactive ingredients

acrylates copolymer, alpha-tocopherol acetate, denatonium benzoate, glycerin, isopropyl myristate, propylene glycol, tert-butyl alcohol, triisopropanolamine, fragrance.